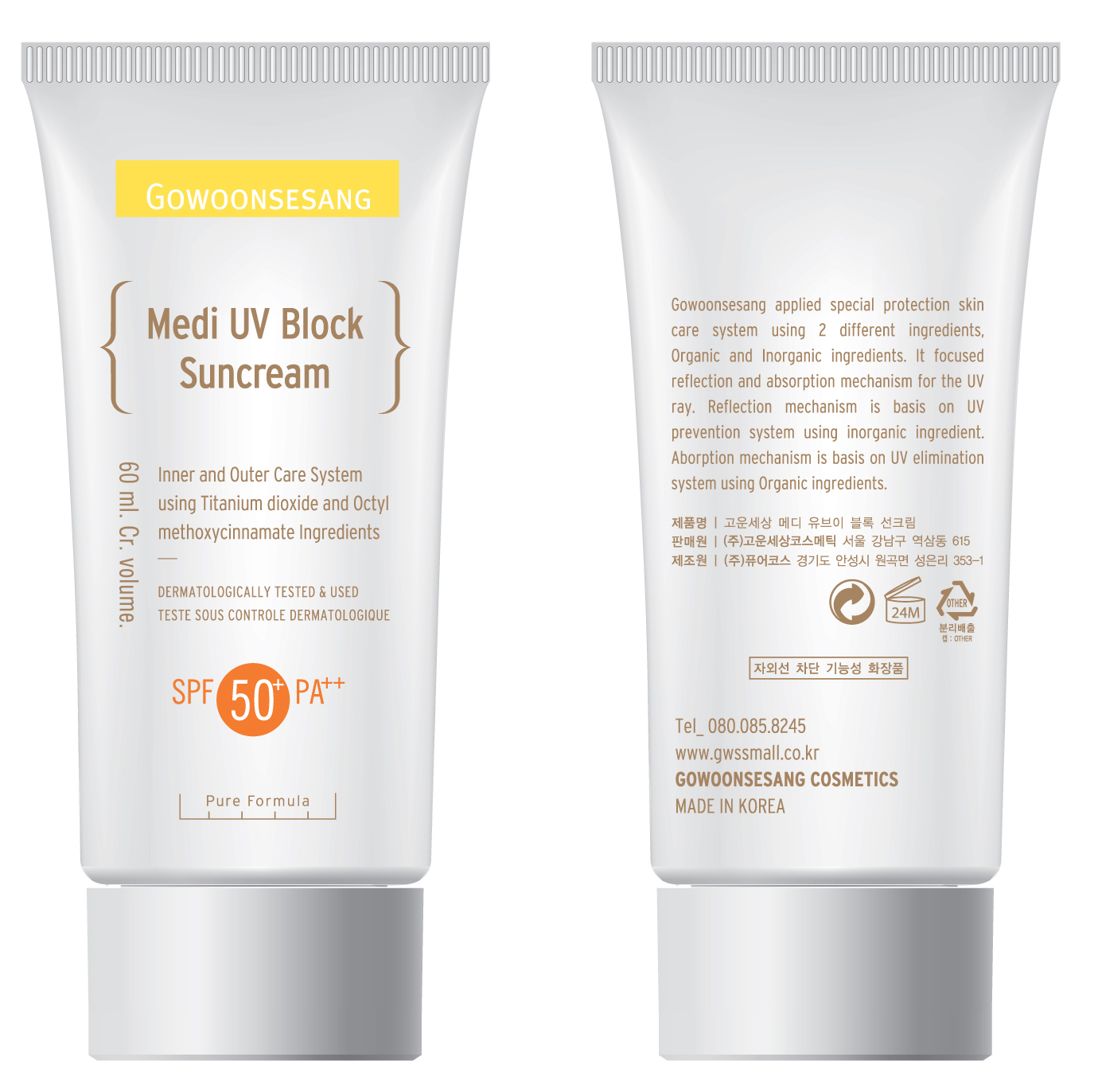 DRUG LABEL: Medi UV Block Suncream SPF50 PA
NDC: 43948-8001 | Form: CREAM
Manufacturer: The Doctor's Cosmetic Inc
Category: otc | Type: HUMAN OTC DRUG LABEL
Date: 20091001

ACTIVE INGREDIENTS: OCTINOXATE 3 mL/60 mL; OCTOCRYLENE 0.6 mL/60 mL

ACTIVE INGREDIENTS:

Ethylhexyl Methoxycinnamate, Sodium Hyaluronate, Octocrylene, Beta-Glucan, Camellia Sinensis Leaf Extract, Scutellaria Baicalensis Root Extract

CAUTION: Keep away from children.

WHEN USING

DIRECTION OF USE:

Use as the end of basic skincare as a finishing step or use at least 30 minutes before going out. Take ample amount of cream and apply evenly on exposed skin by pressing.

PACKAGE LABEL

Label20c